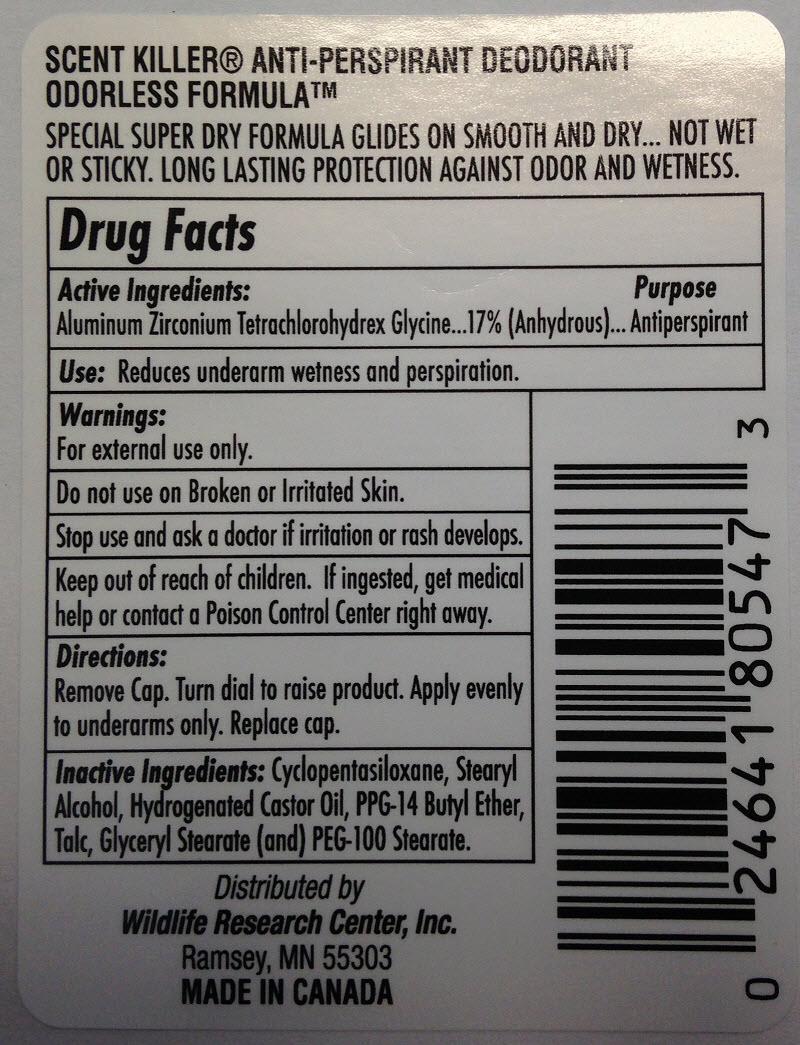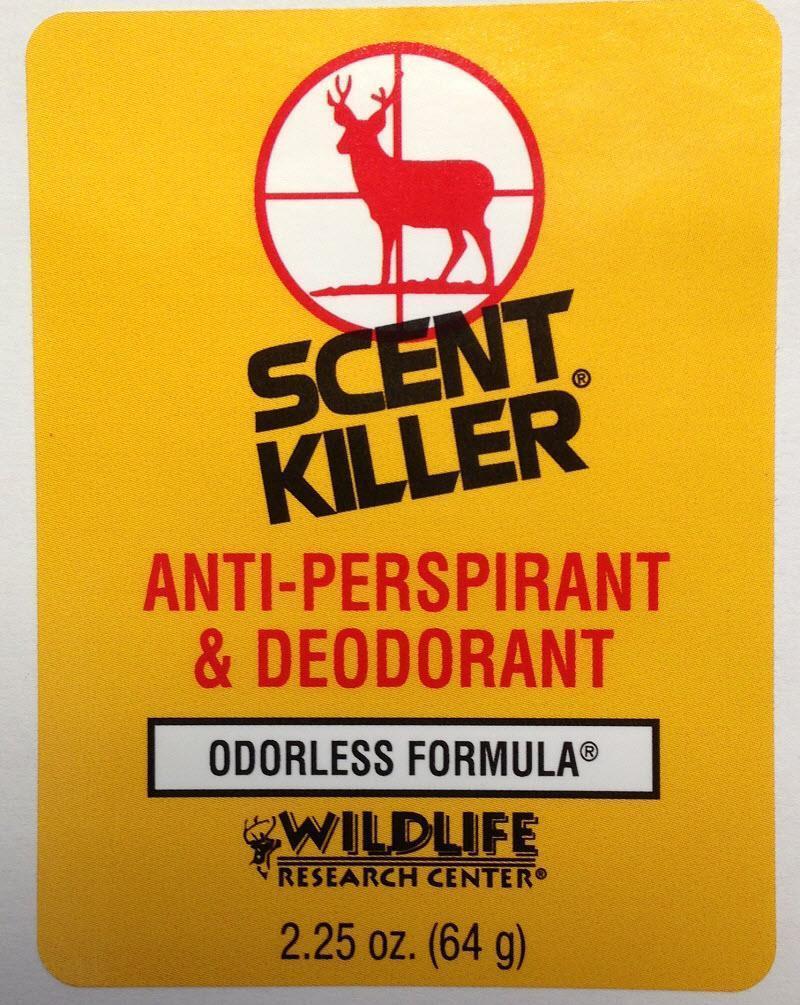 DRUG LABEL: Scent Killer Anti-Perspirant and Deodorant
NDC: 64776-696 | Form: STICK
Manufacturer: Wildlife Research Center, Inc.
Category: otc | Type: HUMAN OTC DRUG LABEL
Date: 20140407

ACTIVE INGREDIENTS: ALUMINUM ZIRCONIUM TETRACHLOROHYDREX GLY 22 g/100 g
INACTIVE INGREDIENTS: CYCLOMETHICONE 5; STEARYL ALCOHOL; Hydrogenated Castor Oil; PPG-14 BUTYL ETHER; TALC; GLYCERYL MONOSTEARATE; PEG-100 STEARATE

Scent Killer Anti-Perspirant And Deodorant

Active Ingredients:

Aluminum Zirconium Tetrachlorohydrex Glycine 17% (anhydrous)

Purpose

Antiperspirant

Use:

Reduces underarm wetness and perspiration.

Warnings:

For external use only.

Do not use on Broken or Irritated Skin.

Stop use and ask a doctor if irritation or rash develops.

KEEP OUT OF REACH OF CHILDREN

Keep out of the reach of children. If ingested, get medical help or contact a Poison Control Center right away.

Directions:

Remove Cap. Turn dial to raise product. Apply evenly to underarms only. Replace cap.

Inactive Ingredients:
Cyclopentasiloxane, Stearyl Alcohol, Hydrogenated Castor Oil, PPG-14 Butyl Ether, Talc, Glyceryl Stearate (and) PEG-100 Stearate.